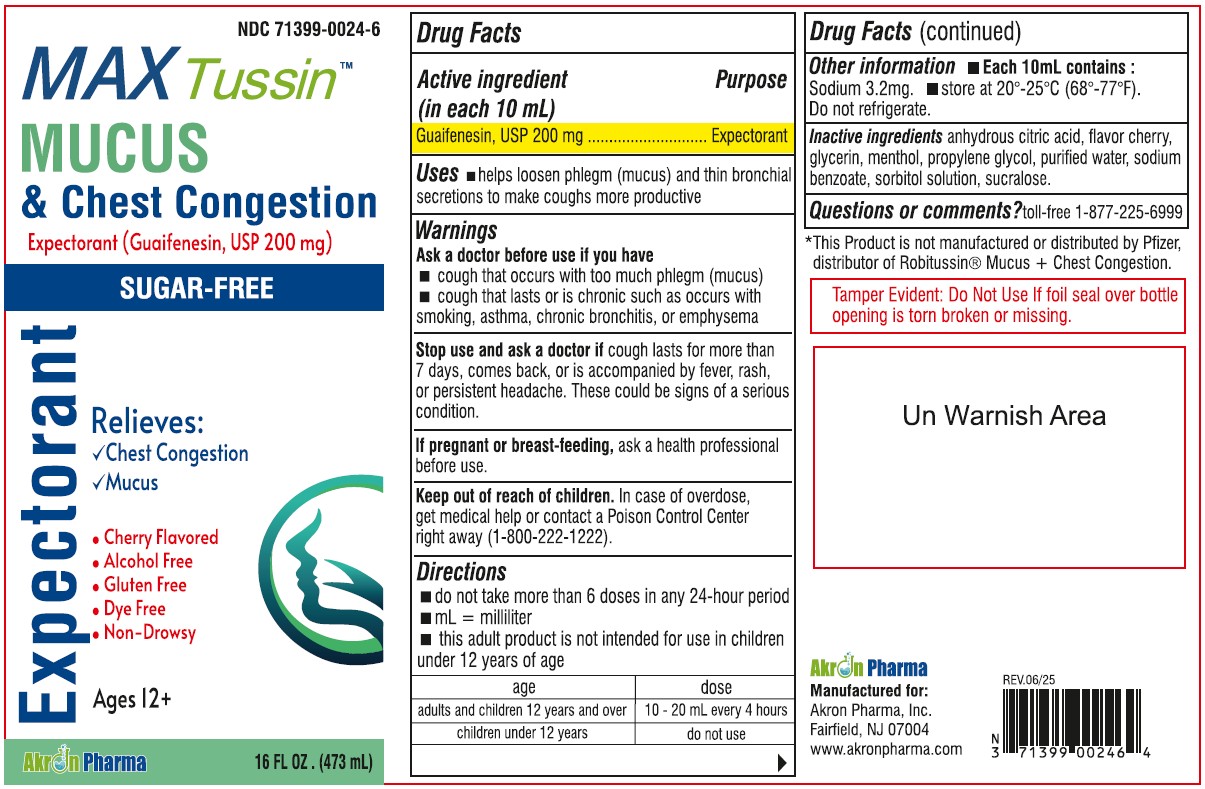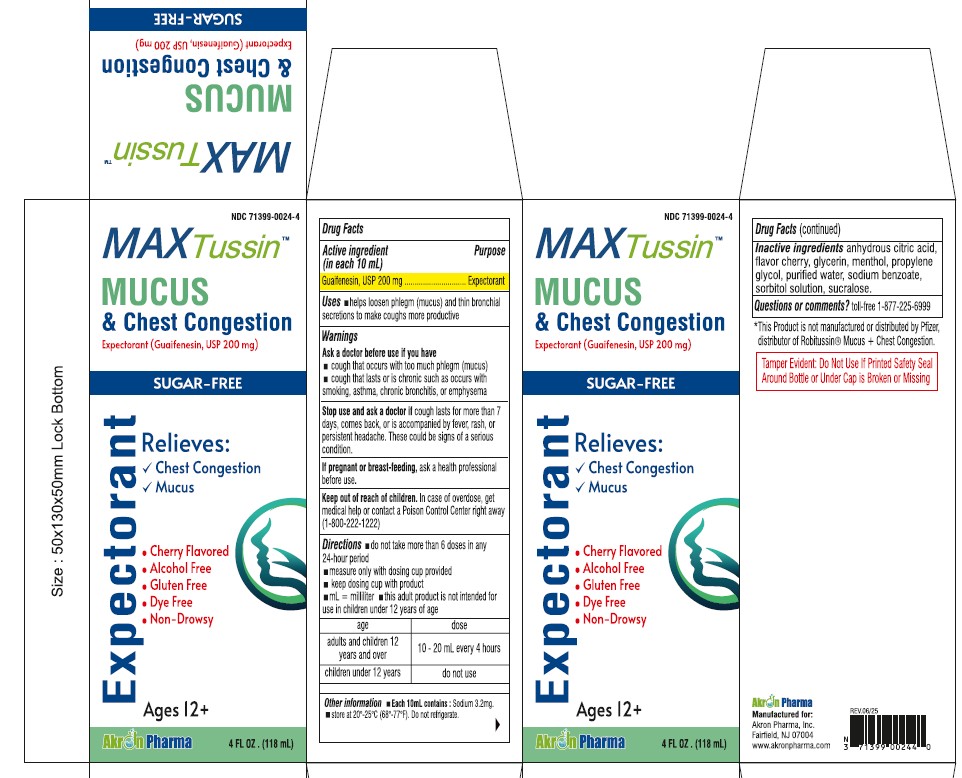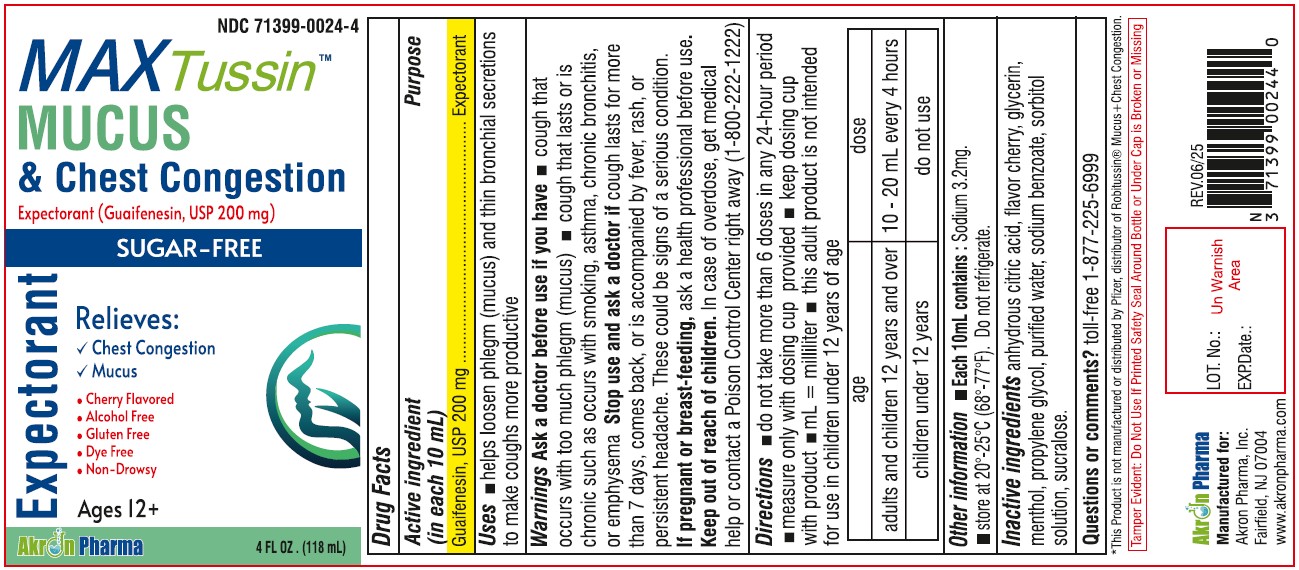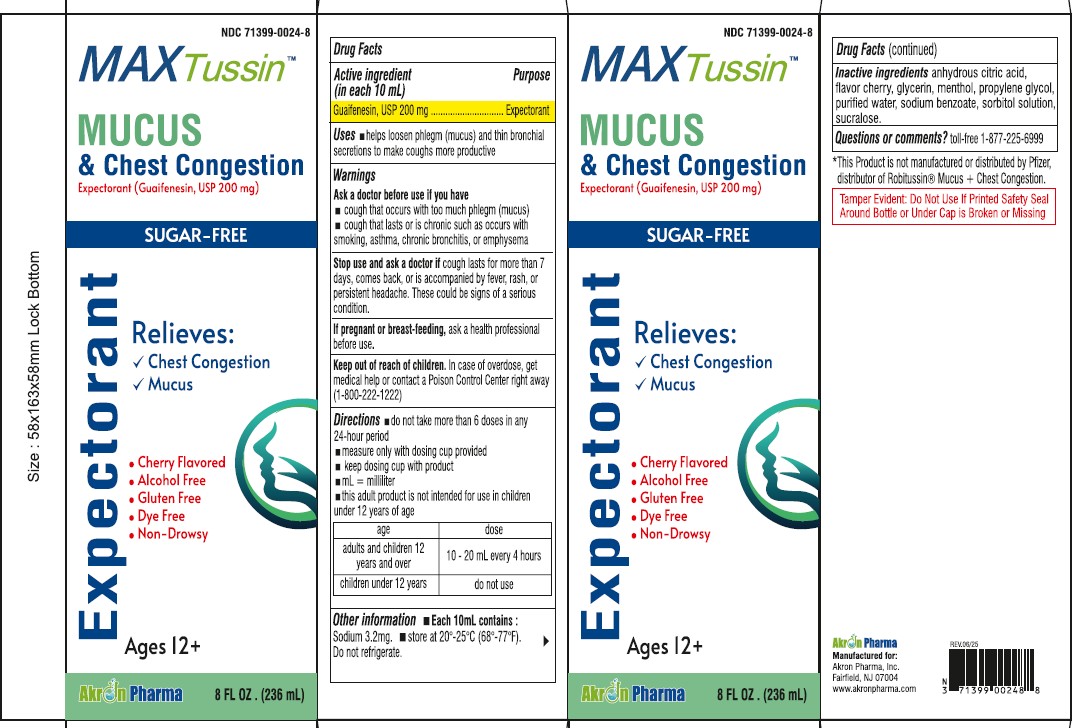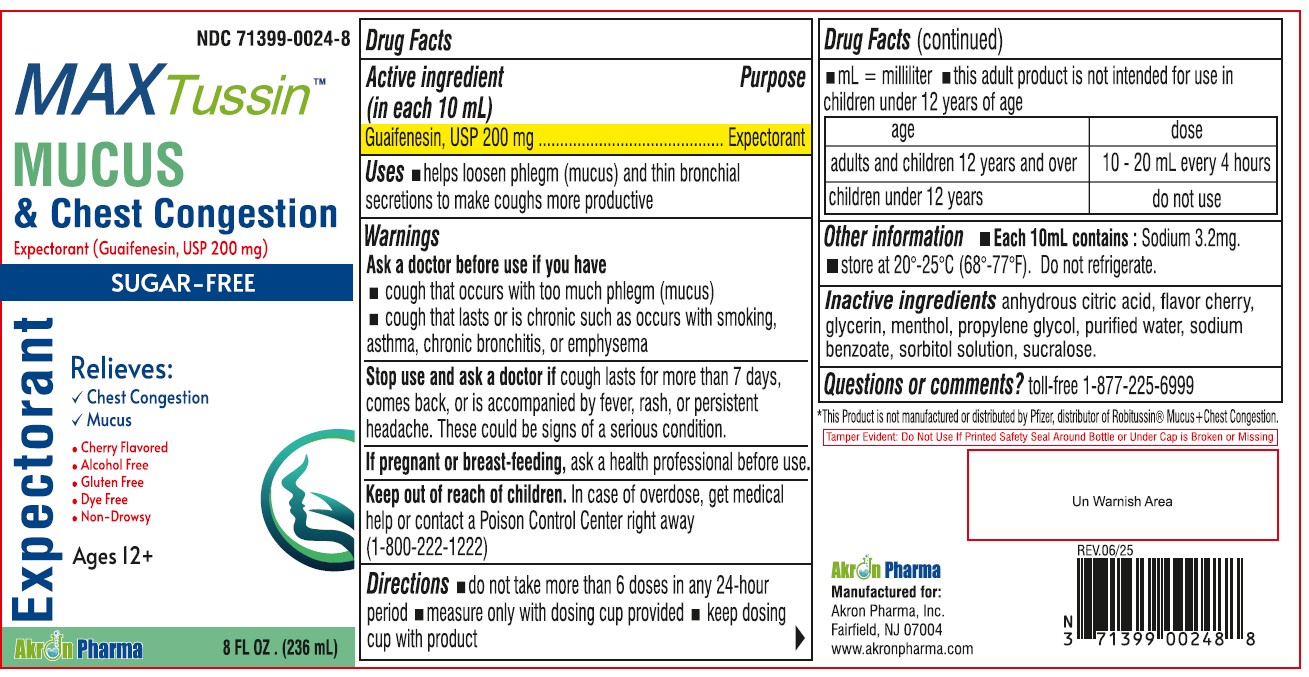 DRUG LABEL: MAX Tussin Mucus and Chest Congestion Sugar Free
NDC: 71399-0024 | Form: LIQUID
Manufacturer: Akron Pharma Inc.
Category: otc | Type: HUMAN OTC DRUG LABEL
Date: 20251027

ACTIVE INGREDIENTS: GUAIFENESIN 200 mg/10 mL
INACTIVE INGREDIENTS: ANHYDROUS CITRIC ACID; GLYCERIN; MENTHOL; WATER; SACCHARIN SODIUM; SODIUM BENZOATE; SORBITOL SOLUTION; SUCRALOSE

Max Tussin Mucus and Chest Congestion
Guaifenesin 200mg per 10ml Oral Solution
Sugar free
Alcohol free
Cherry flavor

Active ingredients (in each 10 mL)

Guaifenesin 200 mg

Purposes

Expectorant

Uses

- helps loosen phlegm (mucus) and thin bronchial secretions to make coughs more productive

Warnings

Ask a doctor before use if you have

- cough that occurs with too much phlegm (mucus)
- cough that lasts or is chronic such as occurs with smoking, asthma, chronic bronchitis or emphysema

Stop use and ask a doctor if

cough lasts more than 7 days, comes back, or is accompanied by fever, rash, or persistent headache. These could be signs of a serious condition.

If pregnant or breast-feeding,

ask a health professional before use.

Keep out of reach of children.

In case of overdose, get medical help or contact a Poison Control Center right away (1-800-222-1222).

Directions

- do not take more than 6 doses in any 24-hour period
- mL= milliliter
- this adult product is not intended for use in children under 12 years of age

age | dose
adults and children 12 years and over | 10 - 20 mL every 4 hours
children under 12 years | do not use

Other information

- Phenylketonurics: contains Phenylalanine 30 mg per 10 mL
- store between 20-25ºC(68-77ºF). Do not refrigerate

Inactive ingredients

anhydrous citric acid, flavor cherry, glycerin, menthol, purified water, saccharin sodium, sodium benzoate, sorbitol solution, sucralose.

Questions or comments?

toll-free 1-877-225-6999

Manufactured for:

Akron Pharma, Inc.

Fairfield, NJ 07004

www.akronpharma.com